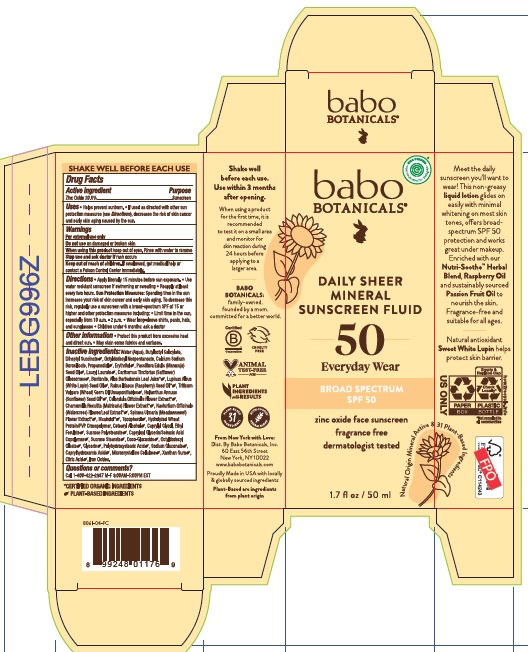 DRUG LABEL: Babo Botanicals Daily Sheer Fluid Mineral Sunscreen SPF 50
NDC: 79265-8061 | Form: LOTION
Manufacturer: Babo Botanicals, Inc.
Category: otc | Type: HUMAN OTC DRUG LABEL
Date: 20240514

ACTIVE INGREDIENTS: ZINC OXIDE 206 mg/1 mL
INACTIVE INGREDIENTS: CITRIC ACID MONOHYDRATE; CELLULOSE, MICROCRYSTALLINE; SUCROSE STEARATE; BUTYLOCTYL SALICYLATE; CAPRYLOYL GLYCERIN/SEBACIC ACID COPOLYMER (2000 MPA.S); OCTYLDODECYL OLEATE; FERRIC OXIDE YELLOW; ALOE VERA LEAF; DIHEPTYL SUCCINATE; CALCIUM ALUMINUM BOROSILICATE; OCTYLDODECYL NEOPENTANOATE; LAURYL LAURATE; PASSIFLORA EDULIS SEED OIL; GLYCERIN; CAPRYLHYDROXAMIC ACID; PROPANEDIOL; CARTHAMUS TINCTORIUS SEED OLEOSOMES; BENTONITE; NASTURTIUM OFFICINALE FLOWERING TOP; POLYHYDROXYSTEARIC ACID (2300 MW); LEVOMENOL; CALENDULA OFFICINALIS FLOWER; CETOSTEARYL ALCOHOL; CHAMOMILE; LUPINUS ALBUS SEED OIL; WHEAT GERM OIL UNSAPONIFIABLES; TOCOPHEROL; FILIPENDULA ULMARIA FLOWER; CAPRYLYL GLYCOL; SUNFLOWER OIL; RASPBERRY SEED OIL; SODIUM GLUCONATE; ETHYL FERULATE; WATER; XANTHAN GUM; COCO GLUCOSIDE; ERYTHRITOL

Babo Botanicals Daily Sheer Fluid Mineral Sunscreen SPF 50

Active ingredient

Zinc Oxide 20.6%

Purpose

Sunscreen

Uses

- Helps prevent sunburn
- If used as directed with other sun protection measures (see Directions), decreases the risk of skin cancer and early skin aging caused by the sun.

Warnings

For external use only

Do not use

on damaged or broken skin

When using this product

keep out of eyes. Rinse with water to remove

Stop use and ask a doctor

if rash occurs

Keep out of reach of children.

If swallowed, get medical help or contact a Poison Control Center immediately.

Directions

- Apply liberally 15 minutes before sun exposure
- Use water resistant sunscreen if swimming or sweating
- Reapply at least every two hours

Sun Protection Measures: Spending time in the sun increases your risk of skin cancer and early skin aging. To decrease this risk, regularly use a sunscreen with a broad-spectrum SPF of 15 or higher and other protection measures including:

- Limit time in the sun, especially from 10 a.m. - 2 p.m.
- Wear long-sleeve shirts, pants, hats, and sunglasses
- Children under 6 months: ask a doctor

Other information

- Protect this product from excessive heat and direct sun.
- May stain some fabrics and surfaces.

Inactive ingredients

Water (Aqua), Butyloctyl Salicylate, Diheptyl Succinate, Octyldodecyl Neopentanoate, Calcium Sodium Borosilicate, Propanediol, Erythritol, Passiflora Edulis (Maracuja) Seed Oil, Lauryl Laurate, Carthamus Tinctorius (Safflower) Oleosomes, Bentonite, Aloe Barbadensis Leaf Juice*, Lupinus Albus (White Lupin) Seed Oil, Rubus Idaeus (Raspberry) Seed Oil*, Triticum Vulgare (Wheat) Germ Oil Unsaponifiables, Helianthus Annuus (Sunflower) Seed Oil*, Calendula Officinalis Flower Extract*, Chamomilla Recutita (Matricaria) Flower Extract*, Nasturtium Officinale (Watercress) Flower/Leaf Extract*, Spiraea Ulmaria (Meadowsweet) Flower Extract*, Bisabolol*, Tocopherol, Hydrolyzed Wheat Protein/PVP Crosspolymer, Cetearyl Alcohol, Caprylyl Glycol, Ethyl Ferulate, Sucrose Polystearate, Capryloyl Glycerin/Sebacic Acid Copolymer, Sucrose Stearate, Coco-Glucoside, Octyldodecyl Oleate, Glycerin, Polyhydroxystearic Acid, Sodium Gluconate, Caprylhydroxamic Acid, Microcrystalline Cellulose, Xanthan Gum, Citric Acid, Iron Oxides.

*Certified Organic Ingredients

Questions or comments?

Call 1-800-422-2987 M-F 9:00AM-5:00PM EST

Company Information

Dist by Babo Botanicals, Inc.

60 East 56th Street New York, NY 10022

www.babobotanicals.com